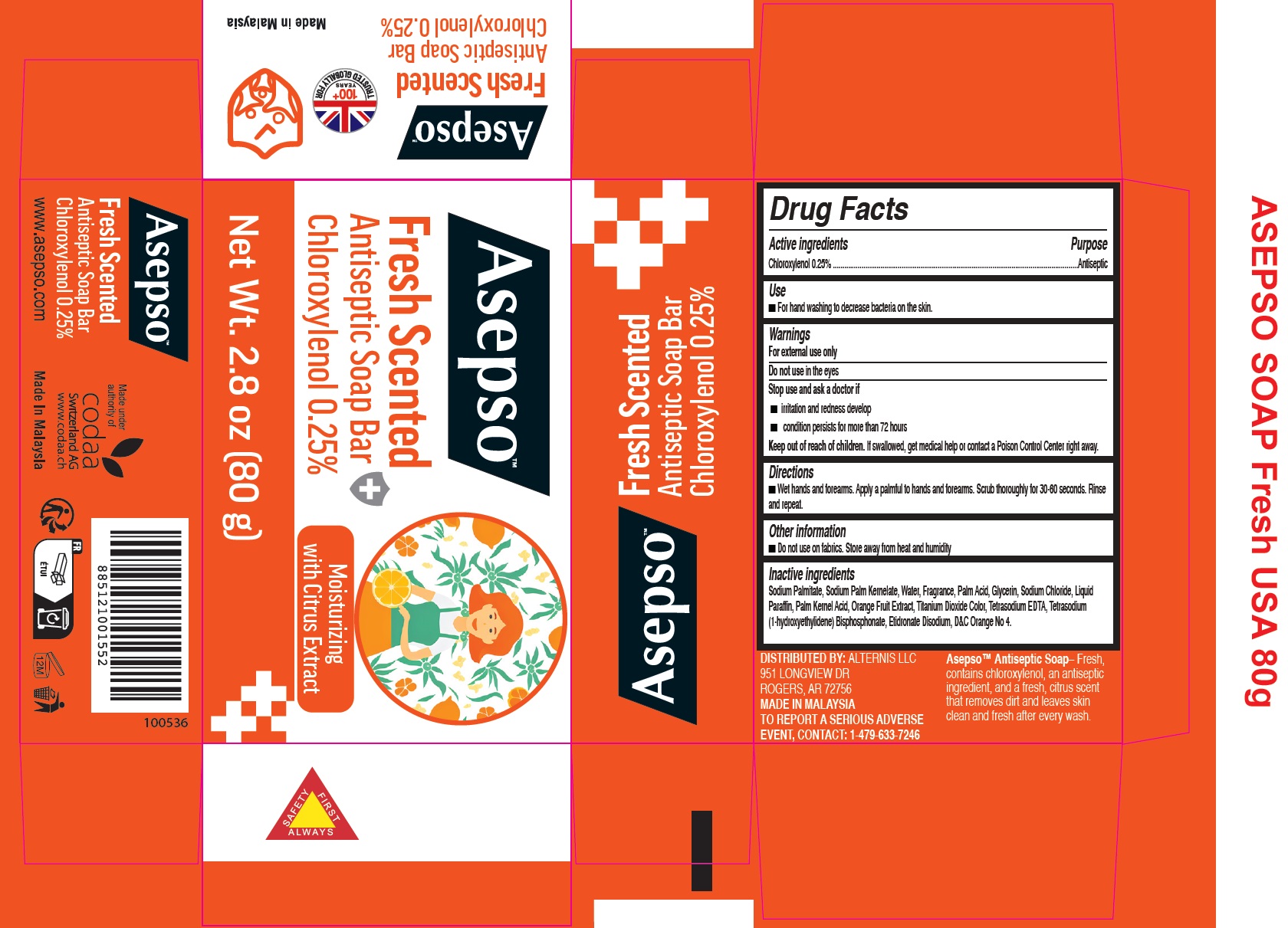 DRUG LABEL: Asepso Fresh Scented Antiseptic
NDC: 49698-008 | Form: SOAP
Manufacturer: CODAA SWITZERLAND AG
Category: otc | Type: HUMAN OTC DRUG LABEL
Date: 20231027

ACTIVE INGREDIENTS: CHLOROXYLENOL 2.5 mg/1 g
INACTIVE INGREDIENTS: SODIUM PALMITATE; SODIUM PALM KERNELATE; WATER; PALM ACID; GLYCERIN; SODIUM CHLORIDE; MINERAL OIL; PALM KERNEL ACID; ORANGE; EDETATE SODIUM; ETIDRONATE DISODIUM; D&C ORANGE NO. 4

Asepso Fresh Scented Antiseptic Soap

Active ingredients

Chloroxylenol 0.25%

Purpose

Antiseptic

Use

- For hand washing to decrease bacteria on the skin.

Warnings

For external use only

Do not use

in the eyes

Stop use and ask a doctor if

- irritation and redness develop
- condition persists for more than 72 hours

Keep out of reach of children.

If swallowed, get medical help or contact a Poison Control Center right away.

Directions

- Wet hands and forearms. Apply a palmful to hands and forearms. Scrub thoroughly for 30-60 seconds. Rinse and repeat.

Other information

- Do not use on fabrics. Store away from heat and humidity

Inactive ingredients

Sodium Palmitate, Sodium Palm Kernelate, Water, Fragrance, Palm Acid, Glycerin, Sodium Chloride, Liquid Paraffin, Palm Kernel Acid, Orange Fruit Extract, Titanium Dioxide Color, Tetrasodium EDTA, Tetrasodium (1-hydroxyethylidene) Bisphosphonate, Etidronate Disodium, D&C Orange No 4.